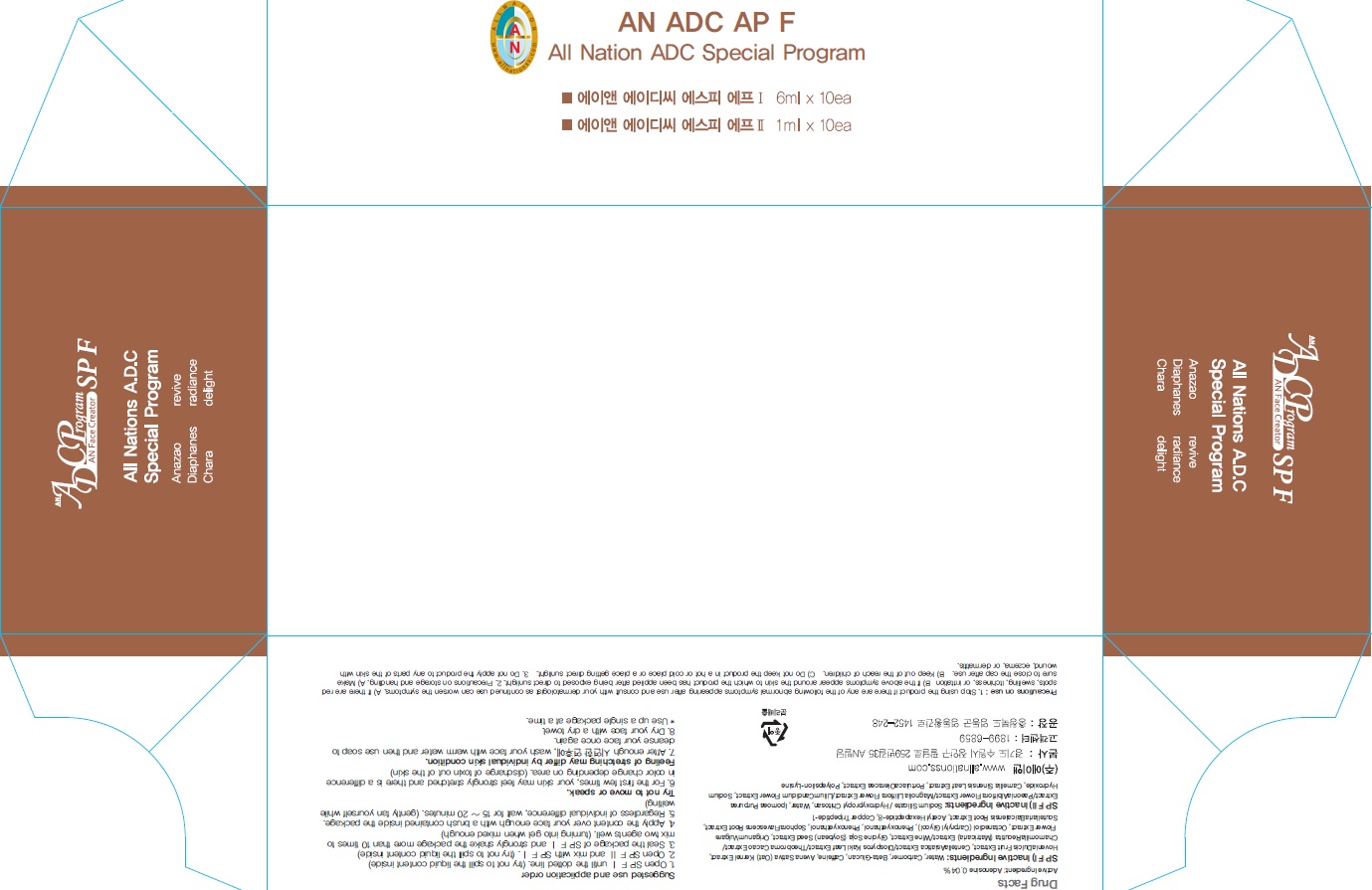 DRUG LABEL: AN ADC SP F
NDC: 69153-070 | Form: SOLUTION
Manufacturer: AN Co Ltd.
Category: otc | Type: HUMAN OTC DRUG LABEL
Date: 20160624

ACTIVE INGREDIENTS: Adenosine 2.8 mg/7 mL
INACTIVE INGREDIENTS: Water

ACTIVE INGREDIENT

Active Ingredient: Adenosine 0.04%

INACTIVE INGREDIENT

SP F I) Inactive Ingredients: Water, Carbomer, Beta-Glucan, Caffeine, Avena Sativa (Oat) Kernel Extract, Hovenia Dulcis Fruit Extract, Centella Asiatica Extract/Diospyros Kaki Leaf Extract/Theobroma Cacao Extract/Chamomilla Recutita (Matricaria) Extract/Wine Extract, Glycine Soja (Soybean) Seed Extract, Origanum Vulgare Flower Extract, Octanediol (Carprylyl Glycol), Phenoxyethanol, Phenoxyethanol, Sophora Flavescens Root Extract, Scutellaria Baicalensis Root Extract, Acetyl Hexapeptide-8, Copper Tripeptide-1

SP F II) Inactive Ingredients: Sodium Silicate / Hydroxypropyl Chitosan, Water, Ipomoea Purpurea Extract/Paeonia Albiflora Flower Extract/Magnolia Liliflora Flower Extract/Lilium Candidum Flower Extract, Sodium Hydroxide, Camellia Sinensis Leaf Extract, Portulaca Oleracea Extract, Polyepsilon-Lysine

PURPOSE

Purpose: Skin Protectant

WARNINGS

Precautions on use: 1. Stop using the product if there are any of the following abnormal symptoms appearing after use and consult with your dermatologist as continued use can worsen the symptoms. A) If there are red spots, swelling, itchiness, or irritation B) If the above symptoms appear around the skin to which the product has been applied after being exposed to direct sunlight. 2. Precautions on storage and handling A) Make sure to close the cap after use. B) Keep out of the reach of children. C) Do not keep the product in a hot or cold place or a place getting direct sunlight. 3. Do not apply the product to any parts of the skin with wound, eczema, or dermatitis.

KEEP OUT OF REACH OF CHILDREN

Suggested use and application order: 1. Open SP F Ⅰ until the dotted line. (try not to spill the liquid content inside) 2. Open SP F Ⅱ and mix with SP F Ⅰ. (try not to spill the liquid content inside) 3. Seal the package of SP F Ⅰ and strongly shake the package more than 10 times to mix two agents well. (turning into gel when mixed enough) 4. Apply the content over your face enough with a brush contained inside the package. 5. Regardless of individual difference, wait for 15 ~ 20 minutes. (gently fan yourself while waiting) Try not to move or speak. 6. For the first few times, your skin may feel strongly stretched and there is a difference in color change depending on area. (discharge of toxin out of the skin) Feeling of stretching may differ by individual skin condition. 7. After enough application, wash your face with warm water and then use soap to cleanse your face once again. 8. Dry your face with a dry towel.

DOSAGE & ADMINISTRATION

Dosage & administration: Use up a single package at a time.